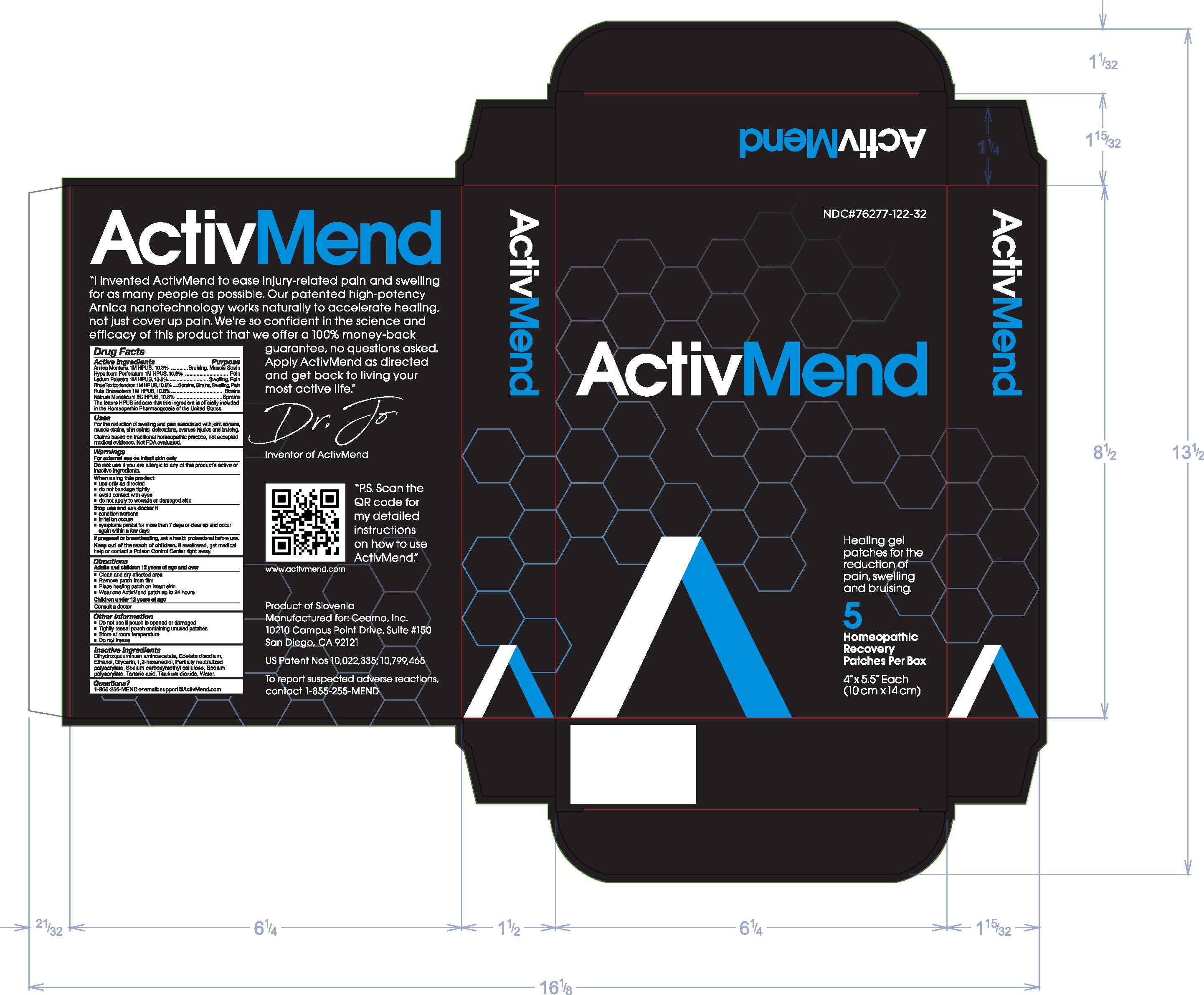 DRUG LABEL: ActivMend
NDC: 76277-122 | Form: PATCH
Manufacturer: Cearna, Inc.
Category: homeopathic | Type: HUMAN OTC DRUG LABEL
Date: 20251223

ACTIVE INGREDIENTS: HYPERICUM PERFORATUM 1 [hp_M]/1 g; TOXICODENDRON PUBESCENS LEAF 1 [hp_M]/1 g; SODIUM CHLORIDE 2 [hp_C]/1 g; LEDUM PALUSTRE TWIG 1 [hp_M]/1 g; ARNICA MONTANA 1 [hp_M]/1 g; RUTA GRAVEOLENS FLOWERING TOP 1 [hp_M]/1 g
INACTIVE INGREDIENTS: ALCOHOL; DIHYDROXYALUMINUM AMINOACETATE; 1,2-HEXANEDIOL; EDETATE DISODIUM; WATER; ACRYLIC ACID/SODIUM ACRYLATE COPOLYMER (1:1; 600 MPA.S AT 0.2%); TARTARIC ACID; SODIUM POLYACRYLATE (8000 MW); CARBOXYMETHYLCELLULOSE SODIUM; GLYCERIN; TITANIUM DIOXIDE

ActivMend

Active ingredients

Arnica Montana 1M HPUS, 10.8%

Hypericum Perforatum 1M HPUS, 10.8%

Ledum Palustre 1M HPUS, 10.8%

Rhus Toxicodendron 1M HPUS, 10.8%

Ruta Graveolens 1M HPUS, 10.8%

Natrum Muraticum 2C HPUS, 10.8%

Purpose

Arnica Montana 1M HPUS, 10.8%................Bruising, Muscle Strain

Hypericum Perforatum 1M HPUS, 10.8%.................Pain

Ledum Palustre 1M HPUS, 10.8%..............Swelling, Pain

Rhus Toxicodendron 1M HPUS, 10.8%................Sprains, Strains, Swelling, Pain

Ruta Graveolens 1M HPUS, 10.8%..............Strains

Natrum Muraticum 2C HPUS, 10.8%......................Sprains

The letter HPUS indicate that this ingredient is officially included in the Homeopathic Pharmacopoeia of the United States.

Uses

For the reduction of swelling and pain associated with joint sprains, muscle strains, dislocations, overuse injuries and bruising.

Claims based on traditional homeopathic practice, not accepted medical evidence. Not FDA evaluated.

Warnings

For external use on intact skin only

Do not use if you are allergic to any of this product's active or inactive ingredients.

When using this product

- use only as directed
- do not bandage tightly
- avoid contact with eyes
- do not apply to wounds or damaged skin

Stop use and ask a doctor if

- condition worsens
- irritation occurs
- symptoms persist for more than 7 days or clear up and occur again within a few days

PREGNANCY OR BREAST FEEDING

I f pregnant or breastfeeding, ask a health professional before use.

Keep out of reach of children. If swallowed, get medical help or contact a Poison Control Center right away.

Directions

Adults and children 12 years of age and over

- Clean and dry affected area
- Remove patch from film
- Place healing patch on intact skin
- Wear one ActivMend patch up to 24 hours.

Children under 12 years of age

Consult a doctor

Other information

- Do not use if pouch is opened or damaged
- Tightly reseal pouch containing unused patches
- Store at room temperature
- Do not freeze

Inactive ingredients

Dihydroxyaluminum aminoacetate, Edetate disodium, Ethanol, Glycerin, 1,2-hexanediol, Partially neutralized polyacrylate, Sodium carboxymethyl cellulose, Sodium polyacrylate, Tartaric acid, Titanium dioxide, Water

Questions?

1-855-255-MEND or email: Support@ActivMend.com

Principal Display Panel

NDC #76277-122-32

ActivMend

Healing gel patches for the reduction of pain, swelling and bruising.

5 Homeopathic Recovery Patches Per Box

4" x 5.5" Each

(10 cm x 14 cm)